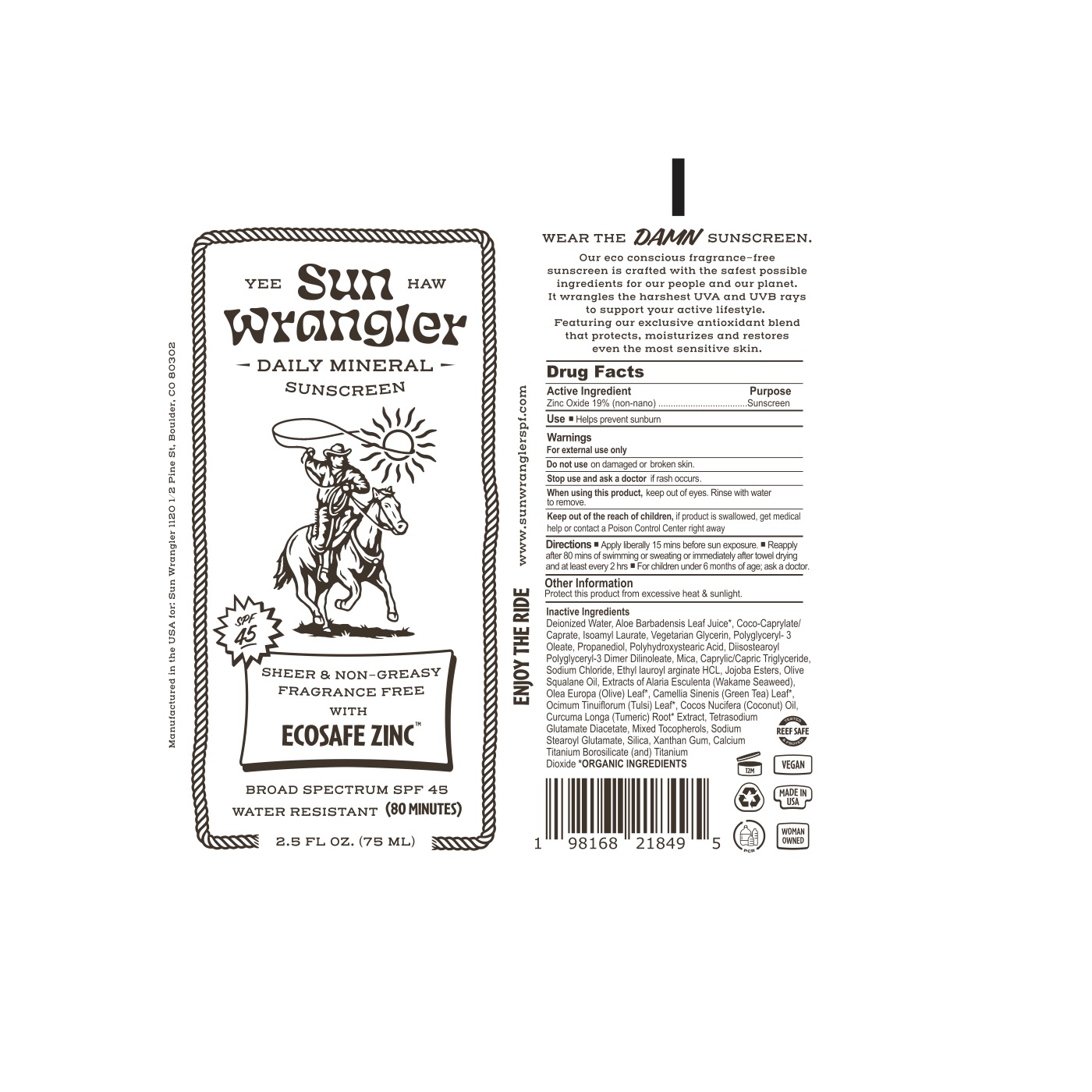 DRUG LABEL: Sun Wrangler Daily Mineral Sunscreen SPF 45
NDC: 84340-045 | Form: CREAM
Manufacturer: Sun Wrangler
Category: otc | Type: HUMAN OTC DRUG LABEL
Date: 20240712

ACTIVE INGREDIENTS: ZINC OXIDE 190 mg/1 mL
INACTIVE INGREDIENTS: WATER; ALOE VERA LEAF; COCO-CAPRYLATE; ISOAMYL LAURATE; GLYCERIN; POLYGLYCERYL-3 OLEATE; PROPANEDIOL; POLYHYDROXYSTEARIC ACID (2300 MW); DIISOSTEAROYL POLYGLYCERYL-3 DIMER DILINOLEATE; MICA; TRICAPRIN; SODIUM CHLORIDE; ETHYL LAUROYL ARGINATE HYDROCHLORIDE; HYDROLYZED JOJOBA ESTERS (ACID FORM); OLIVE OIL; ALARIA ESCULENTA; OLEA EUROPAEA LEAF; GREEN TEA LEAF; HOLY BASIL LEAF; COCONUT OIL; TURMERIC; TETRASODIUM GLUTAMATE DIACETATE; TOCOPHEROL; SODIUM STEAROYL GLUTAMATE; SILICON DIOXIDE; XANTHAN GUM

Sun Wrangler Daily Mineral Sunscreen SPF 45

ACTIVE INGREDIENT

Zinc Oxide 19% (Non-Nano)

PURPOSE

Sunscreen

INDICATIONS AND USAGE

Helps prevent sunburn.

WARNINGS

For external use only.

Do not use on damaged or broken skin.

Stop use and ask a doctor if rash occurs.

When using this product, keep out of eyes. Rinse with water to remove.

KEEP OUT OF REACH OF CHILDREN

If product is swallowed, get medical help or contact a Poison Control Center right away.

DOSAGE AND ADMINISTRATION

- Apply liberally 15 minutes before sun exposure.
- Reapply after 80 minutes of swimming or sweating or immediately after towel drying and at least every 2 hours.
- For children under 6 months of age; ask a doctor.

OTHER SAFETY INFORMATION

Protect this product from excessive heat and sunlight.

INACTIVE INGREDIENT

Deionized Water, Aloe Barbadensis Leaf Juice*, Coco-Caprylate/Caprate, Isoamyl Laurate, Vegetarian Glycerin, Polyglyceryl- 3 Oleate, Propanediol, Polyhydroxystearic Acid, Diisostearoyl Polyglyceryl- 3 Dimer Dinoleate, Mica, Caprylic/Capric Triglyceride, Sodium Chloride, Ethyl lauroyl arginate HCl, Jojoba Esters, Olive Squalane Oil, Extracts of Alaria Esculenta (Wakame Seaweed), Olea Europa (Olive) Leaf*, Camellia Sinenis (Green Tea) Leaf*, Ocimum Tinuiflorum (Tulsi) Leaf*, Cocos Nucifera (Coconut) Oil, Curcuma Longa (Turmeric) Root* Extract, Tetrasodium Glutamate Diacetate, Mixed Tocopherols, Sodium Stearoyl Glutamate, Silica, Xanthan Gum, Calcium Titanium Borosilicate and Titanium.